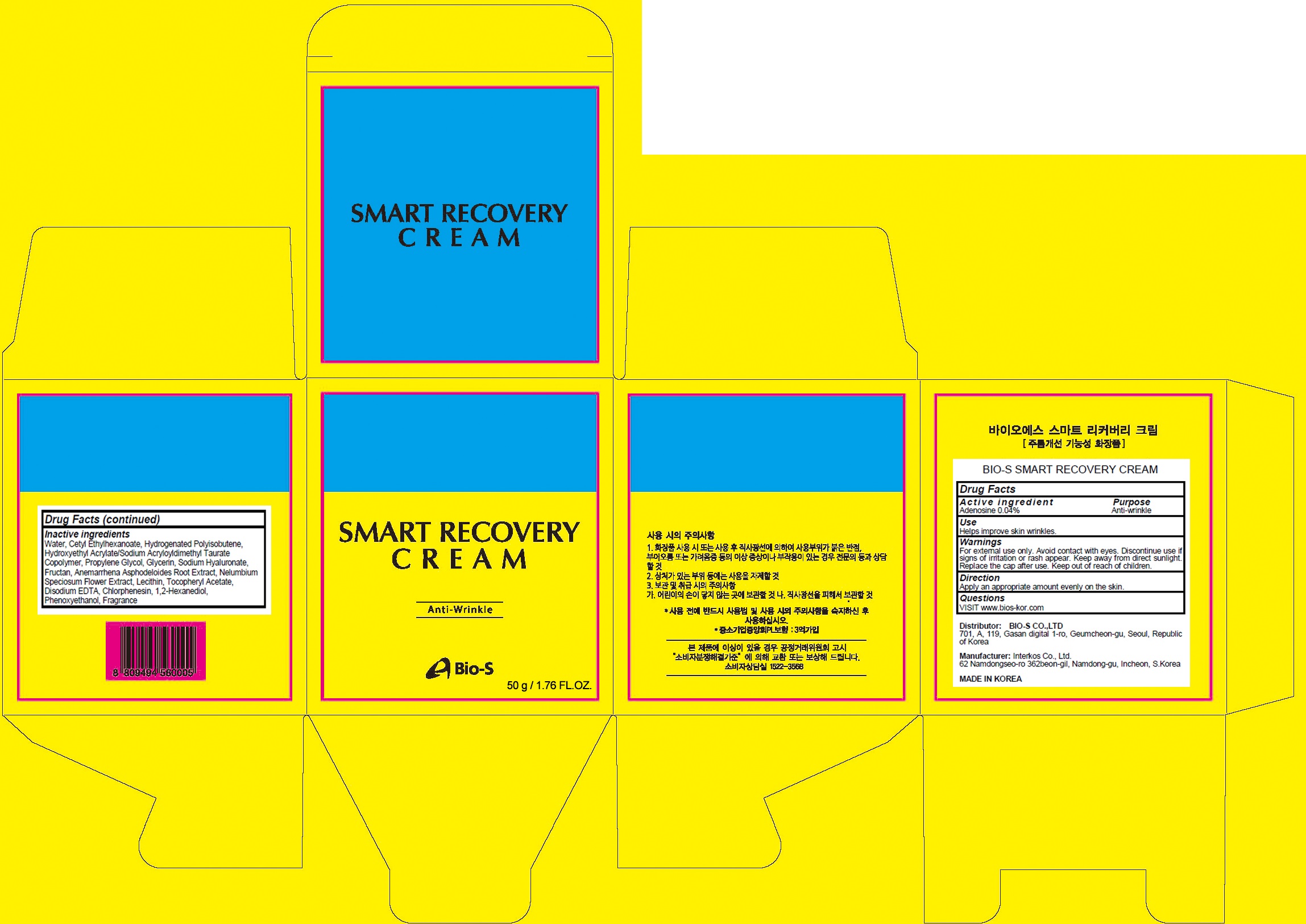 DRUG LABEL: SMART RECOVERY
NDC: 81211-020 | Form: CREAM
Manufacturer: BIO-S CO.,LTD
Category: otc | Type: HUMAN OTC DRUG LABEL
Date: 20201210

ACTIVE INGREDIENTS: Adenosine 0.02 g/50 g
INACTIVE INGREDIENTS: Water; Cetyl Ethylhexanoate; HYDROGENATED POLYBUTENE (1300 MW); HYDROXYETHYL ACRYLATE/SODIUM ACRYLOYLDIMETHYL TAURATE COPOLYMER (100000 MPA.S AT 1.5%); Propylene Glycol

ACTIVE INGREDIENT

Adenosine 0.04%

PURPOSE

Anti-wrinkle

Use

Helps improve skin wrinkles.

WARNINGS

For external use only.
Avoid contact with eyes.
Discontinue use if signs of irritation or rash appear.
Keep away from direct sunlight.
Replace the cap after use.
Keep out of reach of children.

KEEP OUT OF REACH OF CHILDREN

Direction

Apply an appropriate amount evenly on the skin.

QUESTIONS

VISIT www.bios-kor.com

INACTIVE INGREDIENTS

Water, Cetyl Ethylhexanoate, Hydrogenated Polyisobutene, Hydroxyethyl Acrylate/Sodium Acryloyldimethyl Taurate Copolymer, Propylene Glycol, Glycerin, Sodium Hyaluronate, Fructan, Anemarrhena Asphodeloides Root Extract, Nelumbium Speciosum Flower Extract, Lecithin, Tocopheryl Acetate, Disodium EDTA, Chlorphenesin, 1,2-Hexanediol, Phenoxyethanol, Fragrance